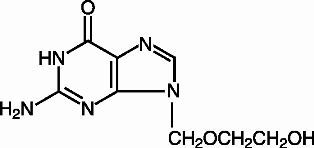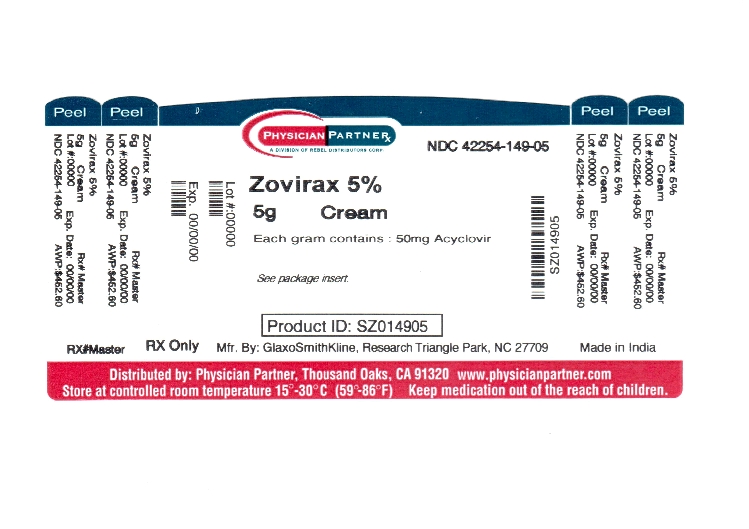 DRUG LABEL: ZOVIRAX
NDC: 42254-149 | Form: CREAM
Manufacturer: Rebel Distributors Corp
Category: prescription | Type: HUMAN PRESCRIPTION DRUG LABEL
Date: 20120209

ACTIVE INGREDIENTS: ACYCLOVIR 50 mg/1 g
INACTIVE INGREDIENTS: CETOSTEARYL ALCOHOL; MINERAL OIL; POLOXAMER 407; PROPYLENE GLYCOL; SODIUM LAURYL SULFATE; WATER; PETROLATUM

ZOVIRAX®
(acyclovir)
Cream 5%
USE ONLY FOR COLD SORES

DESCRIPTION

ZOVIRAX is the brand name for acyclovir, a synthetic nucleoside analogue active against herpesviruses. ZOVIRAX Cream 5% is a formulation for topical administration. Each gram of ZOVIRAX Cream 5% contains 50 mg of acyclovir and the following inactive ingredients: cetostearyl alcohol, mineral oil, poloxamer 407, propylene glycol, sodium lauryl sulfate, water, and white petrolatum.

Acyclovir is a white, crystalline powder with the molecular formula C8H11N5O3 and a molecular weight of 225. The maximum solubility in water at 37°C is 2.5 mg/mL. The pKa’s of acyclovir are 2.27 and 9.25.

The chemical name of acyclovir is 2-amino-1,9-dihydro-9-[(2-hydroxyethoxy)methyl]-6H-purin-6-one; it has the following structural formula:

VIROLOGY

Mechanism of Antiviral Action:

Acyclovir is a synthetic purine nucleoside analogue with in vitro and in vivo inhibitory activity against herpes simplex virus types 1 (HSV-1), 2 (HSV-2), and varicella-zoster virus (VZV).

The inhibitory activity of acyclovir is highly selective due to its affinity for the enzyme thymidine kinase (TK) encoded by HSV and VZV. This viral enzyme converts acyclovir into acyclovir monophosphate, a nucleotide analogue. The monophosphate is further converted into diphosphate by cellular guanylate kinase and into triphosphate by a number of cellular enzymes. In vitro, acyclovir triphosphate stops replication of herpes viral DNA. This is accomplished in 3 ways: 1) competitive inhibition of viral DNA polymerase, 2) incorporation into and termination of the growing viral DNA chain, and 3) inactivation of the viral DNA polymerase. The greater antiviral activity of acyclovir against HSV compared with VZV is due to its more efficient phosphorylation by the viral TK.

Antiviral Activities:

The quantitative relationship between the in vitro susceptibility of herpes viruses to antivirals and the clinical response to therapy has not been established in humans, and virus sensitivity testing has not been standardized. Sensitivity testing results, expressed as the concentration of drug required to inhibit by 50% the growth of virus in cell culture (IC50), vary greatly depending upon a number of factors. Using plaque-reduction assays, the IC50 against herpes simplex virus isolates ranges from 0.02 to 13.5 mcg/mL for HSV-1 and from 0.01 to 9.9 mcg/mL for HSV-2. The IC50 for acyclovir against most laboratory strains and clinical isolates of VZV ranges from 0.12 to 10.8 mcg/mL. Acyclovir also demonstrates activity against the Oka vaccine strain of VZV with a mean IC50 of 1.35 mcg/mL.

Drug Resistance:

Resistance of HSV and VZV to acyclovir can result from qualitative and quantitative changes in the viral TK and/or DNA polymerase. Clinical isolates of HSV and VZV with reduced susceptibility to acyclovir have been recovered from immunocompromised patients, especially with advanced HIV infection. While most of the acyclovir-resistant mutants isolated thus far from immunocompromised patients have been found to be TK-deficient mutants, other mutants involving the viral TK gene (TK partial and TK altered) and DNA polymerase have been isolated. TK-negative mutants may cause severe disease in infants and immunocompromised adults. The possibility of viral resistance to acyclovir should be considered in patients who show poor clinical response during therapy.

CLINICAL PHARMACOLOGY

Pharmacokinetics:

Adults:

A clinical pharmacology study was performed with ZOVIRAX Cream in adult volunteers to evaluate the percutaneous absorption of acyclovir. In this study, which included 6 male volunteers, the cream was applied to an area of 710 cm^2 on the backs of the volunteers 5 times daily at intervals of 2 hours for a total of 4 days. The weight of cream applied and urinary excretion of acyclovir were measured daily. Plasma concentration of acyclovir was assayed 1 hour after the final application. The average daily urinary excretion of acyclovir was approximately 0.04% of the daily applied dose. Plasma acyclovir concentrations were below the limit of detection (0.01 μM) in 5 subjects and barely detectable (0.014 μM) in 1 subject. Systemic absorption of acyclovir from ZOVIRAX Cream is minimal in adults.

Pediatric Patients:

The systemic absorption of acyclovir following topical application of cream has not been evaluated in patients <18 years of age.

CLINICAL TRIALS

Adults:

ZOVIRAX Cream was evaluated in 2 double-blind, randomized, placebo (vehicle)-controlled trials for the treatment of recurrent herpes labialis. The average patient had 5 episodes of herpes labialis in the previous 12 months. In the first study, median age was 37 years (range 18 to 81 years), 74% were female, and 94% were Caucasian. In the second study, median age was 38 years (range 18 to 87 years), 73% were female, and 94% were Caucasian. Subjects were instructed to initiate treatment within 1 hour of noticing signs or symptoms and continue treatment for 4 days, with application of study medication 5 times per day. In both studies, the mean duration of the recurrent herpes labialis episode was approximately one-half day shorter in the subjects treated with ZOVIRAX Cream (n = 682) compared with subjects treated with placebo (n = 703) (approximately 4.5 days versus 5 days, respectively). No significant difference was observed between subjects receiving ZOVIRAX Cream or vehicle in the prevention of progression of cold sore lesions.

Pediatric Patients:

An open-label, uncontrolled trial with ZOVIRAX Cream 5% was conducted in 113 patients aged 12 to 17 years with herpes labialis. In this study, therapy was applied using the same dosing regimen as in adults and subjects were followed for adverse events. The safety profile was similar to that observed in adults.

INDICATIONS AND USAGE

ZOVIRAX Cream is indicated for the treatment of recurrent herpes labialis (cold sores) in adults and adolescents (12 years of age and older).

CONTRAINDICATIONS

ZOVIRAX Cream is contraindicated in patients with known hypersensitivity to acyclovir, valacyclovir, or any component of the formulation.

PRECAUTIONS

General:

ZOVIRAX Cream is intended for cutaneous use only and should not be used in the eye or inside the mouth or nose. ZOVIRAX Cream should only be used on herpes labialis on the affected external aspects of the lips and face. Because no data are available, application to human mucous membranes is not recommended. ZOVIRAX Cream has a potential for irritation and contact sensitization (see ADVERSE REACTIONS). The effect of ZOVIRAX Cream has not been established in immunocompromised patients.

Information for Patients:

Please see Patient Information About ZOVIRAX Cream.

Drug Interactions:

Clinical experience has identified no interactions resulting from topical or systemic administration of other drugs concomitantly with ZOVIRAX Cream.

Carcinogenesis, Mutagenesis, Impairment of Fertility:

Systemic exposure following topical administration of acyclovir is minimal. Dermal carcinogenicity studies were not conducted. Results from the studies of carcinogenesis, mutagenesis and fertility are not included in the full prescribing information for ZOVIRAX Cream due to the minimal exposures of acyclovir that result from dermal application. Information on these studies is available in the full prescribing information for ZOVIRAX Capsules, Tablets, and Suspension and ZOVIRAX for Injection.

Pregnancy:

Teratogenic Effects:

Pregnancy Category B. Acyclovir was not teratogenic in the mouse, rabbit, or rat at exposures greatly in excess of human exposure. There are no adequate and well-controlled studies of systemic acyclovir in pregnant women. A prospective epidemiologic registry of acyclovir use during pregnancy was established in 1984 and completed in April 1999. There were 749 pregnancies followed in women exposed to systemic acyclovir during the first trimester of pregnancy resulting in 756 outcomes. The occurrence rate of birth defects approximates that found in the general population. However, the small size of the registry is insufficient to evaluate the risk for less common defects or to permit reliable or definitive conclusions regarding the safety of acyclovir in pregnant women and their developing fetuses. Systemic acyclovir should be used during pregnancy only if the potential benefit justifies the potential risk to the fetus.

Nursing Mothers:

It is not known whether topically applied acyclovir is excreted in breast milk. Systemic exposure following topical administration is minimal.

After oral administration of ZOVIRAX, acyclovir concentrations have been documented in breast milk in 2 women and ranged from 0.6 to 4.1 times the corresponding plasma levels. These concentrations would potentially expose the nursing infant to a dose of acyclovir up to 0.3 mg/kg/day. Nursing mothers who have active herpetic lesions near or on the breast should avoid nursing.

Geriatric Use:

Clinical studies of acyclovir cream did not include sufficient numbers of subjects aged 65 and over to determine whether they respond differently from younger subjects. Other reported clinical experience has not identified differences in responses between the elderly and younger patients. Systemic absorption of acyclovir after topical administration is minimal (see CLINICAL PHARMACOLOGY).

Pediatric Use:

Safety and effectiveness in pediatric patients less than 12 years of age have not been established.

ADVERSE REACTIONS

In 5 double-blind, placebo-controlled trials, 1,124 patients were treated with ZOVIRAX Cream and 1,161 with placebo (vehicle) cream. ZOVIRAX Cream was well tolerated; 5% of patients on ZOVIRAX Cream and 4% of patients on placebo reported local application site reactions.

The most common adverse reactions at the site of topical application were dry lips, desquamation, dryness of skin, cracked lips, burning skin, pruritus, flakiness of skin, and stinging on skin; each event occurred in less than 1% of patients receiving ZOVIRAX Cream and vehicle. Three patients on ZOVIRAX Cream and 1 patient on placebo discontinued treatment due to an adverse event.

An additional study, enrolling 22 healthy adults, was conducted to evaluate the dermal tolerance of ZOVIRAX Cream compared with vehicle using single occluded and semi-occluded patch testing methodology. Both ZOVIRAX Cream and vehicle showed a high and cumulative irritation potential. Another study, enrolling 251 healthy adults, was conducted to evaluate the contact sensitization potential of ZOVIRAX Cream using repeat insult patch testing methodology. Of 202 evaluable subjects, possible cutaneous sensitization reactions were observed in the same 4 (2%) subjects with both ZOVIRAX Cream and vehicle, and these reactions to both ZOVIRAX Cream and vehicle were confirmed in 3 subjects upon rechallenge. The sensitizing ingredient(s) has not been identified.

The safety profile in patients 12 to 17 years of age was similar to that observed in adults.

Observed During Clinical Practice:

In addition to adverse events reported from clinical trials, the following events have been identified during post-approval use of acyclovir cream. Because they are reported voluntarily from a population of unknown size, estimates of frequency cannot be made. These events have been chosen for inclusion due to a combination of their seriousness, frequency of reporting, or potential causal connection to acyclovir cream.

General:

Angioedema, anaphylaxis.

Skin:

Contact dermatitis, eczema, application site reactions including signs and symptoms of inflammation.

OVERDOSAGE

Overdosage by topical application of ZOVIRAX Cream is unlikely because of minimal systemic exposure (see CLINICAL PHARMACOLOGY).

DOSAGE AND ADMINISTRATION

ZOVIRAX Cream should be applied 5 times per day for 4 days. Therapy should be initiated as early as possible following onset of signs and symptoms (i.e., during the prodrome or when lesions appear). For adolescents 12 years of age and older, the dosage is the same as in adults.

HOW SUPPLIED

Each gram of ZOVIRAX Cream 5% contains 50 mg acyclovir in an aqueous cream base. ZOVIRAX Cream is supplied as follows:

5-g tubes (NDC 42254-149-05).

Store at or below 25°C (77°F); excursions permitted to 15° to 30°C (59° to 86°F) (see USP Controlled Room Temperature).

Manufactured by

GlaxoSmithKline
Research Triangle Park, NC 27709

for

BTA Pharmaceuticals, Inc. (subsidiary of Biovail Corporation)
Bridgewater, NJ 08807

©2009, GlaxoSmithKline. All rights reserved.

July 2009 ZVC:2PI

Repackaged by:

Rebel Distributors Corp
Thousand Oaks, CA 91320

PATIENT INFORMATION ABOUT ZOVIRAX® (ACYCLOVIR) CREAM 5%

USE ONLY FOR COLD SORES. FOR EXTERNAL USE ONLY.

Read this information before you start using ZOVIRAX (acyclovir) Cream and each time you refill your prescription. There may be new information. This summary is not meant to take the place of your doctor's advice.

What is ZOVIRAX Cream?

ZOVIRAX Cream is a prescription medicine that is applied to the skin to treat cold sores (herpes labialis) that occur on the face or lips. However, ZOVIRAX Cream is not a cure for cold sores.

Who should not use ZOVIRAX Cream?

Do not use ZOVIRAX Cream if you are allergic to ZOVIRAX (also known as acyclovir), VALTREX® (also known as valacyclovir), or any of the ingredients of ZOVIRAX Cream. Ask your doctor or pharmacist about the inactive ingredients.

Before you start using ZOVIRAX Cream, tell your doctor if you are pregnant, planning to become pregnant, or are breast feeding.

The safety and efficacy of ZOVIRAX Cream have not been studied in patients younger than 12 years of age or in patients whose immune system is not normal.

How do I use ZOVIRAX Cream?

ZOVIRAX Cream is most effective when used early, at the start of a cold sore. For best results, apply the cream at the first sign of a cold sore (such as tingle, redness, bump, or itch).

- Wash your hands before using ZOVIRAX Cream.
- Apply ZOVIRAX Cream to clean, dry skin.
- Apply a layer of ZOVIRAX Cream to cover only the cold sore or cover only the area of tingling (or other symptoms) before the cold sore appears. Rub the cream in until it disappears.
- Apply the cream 5 times a day for 4 days.
- Wash your hands with soap and water after applying ZOVIRAX Cream. This should remove any cream left on the hands.

What Should I Avoid While Using ZOVIRAX Cream?

- Use ZOVIRAX Cream only on your affected skin. Do not swallow ZOVIRAX Cream. Do not apply ZOVIRAX Cream to the eyes, inside the mouth or nose, or on unaffected skin. Do not use ZOVIRAX Cream for genital herpes.
- Do not cover the cold sore area with a bandage or dressing unless otherwise instructed by your doctor.
- Do not apply another type of skin product (for example, cosmetics, sun screens, or lip balms) or other skin medication to the cold sore area while using ZOVIRAX Cream unless otherwise instructed by your doctor.
- Avoid irritation of the cold sore area while using ZOVIRAX Cream.
- Do not bathe, shower, or swim right after applying ZOVIRAX Cream. This could wash off the medicine.

What Are the Possible Side Effects of ZOVIRAX Cream?

ZOVIRAX Cream was well tolerated in studies in patients with cold sores. The most common skin-related side effects of ZOVIRAX Cream are dry or cracked lips, flakiness or dryness of skin, a burning or stinging feeling, or itching of the skin. Each event occurred in fewer than 1 in 100 patients in clinical studies. Ask a doctor or pharmacist about any concerns about ZOVIRAX Cream.

How Should I Store ZOVIRAX Cream?

Store ZOVIRAX Cream at room temperature (59° to 86°F). Never leave ZOVIRAX Cream in your car in cold or hot weather. Make sure the cap on the tube is tightly closed. Keep ZOVIRAX Cream out of the reach of children.

General Advice about Prescription Medicines

Do not use ZOVIRAX Cream for a condition for which it was not prescribed. Do not give ZOVIRAX Cream to other people, even if they have the same symptoms you have. If you have any concerns about ZOVIRAX Cream, ask your doctor. Your doctor or pharmacist can give you additional information about ZOVIRAX Cream that was written for healthcare professionals.

Manufactured by

GlaxoSmithKline
Research Triangle Park, NC 27709

for

BTA Pharmaceuticals, Inc. (subsidiary of Biovail Corporation)
Bridgewater, NJ 08807

©2009, GlaxoSmithKline. All rights reserved.

July 2009 ZVC:2PIL

Repackaged by:

Rebel Distributors Corp
Thousand Oaks, CA 91320